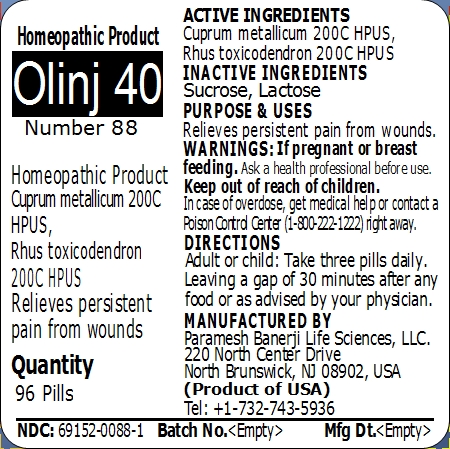 DRUG LABEL: Olinj 40 Number 88
NDC: 69152-0088 | Form: PELLET
Manufacturer: Paramesh Banerji Life Sciences LLC
Category: homeopathic | Type: HUMAN OTC DRUG LABEL
Date: 20150213

ACTIVE INGREDIENTS: COPPER 200 [hp_C]/1 1; TOXICODENDRON PUBESCENS LEAF 200 [hp_C]/1 1
INACTIVE INGREDIENTS: SUCROSE; LACTOSE

Active Ingredients

Cuprum metallicum 200C HPUS, Rhus toxicodendron 200C HPUS

Inactive Ingredients

Sucrose, Lactose

Purpose

Relieves persistent pain from wounds

Uses

Relieves persistent pain from wounds

Warnings

If pregnant or breast feeding ask a health professional before use.

Keep out of reach of children. In case of overdose, get medical help or contact a Poison Control Center (1-800-222-1222) right away.

Direction

Adult or child: Take three pills daily. Leaving a gap of 30 minutes after any food or as advised by your physician.

Manufactured by

Paramesh Banerji Life Sciences, LLC

220 North Center Drive

North Brunswick, NJ 08902, USA

Product of USA

Tel: +1-732-743-5936

Principal Display Panel

Homeopathic Product

Olinj 40

Number 88

Homeopathic Product

Cuprum metallicum 200C HPUS, Rhus toxicodendron 200C HPUS

Relieves persistent pain from wounds

Quantity

96 Pills